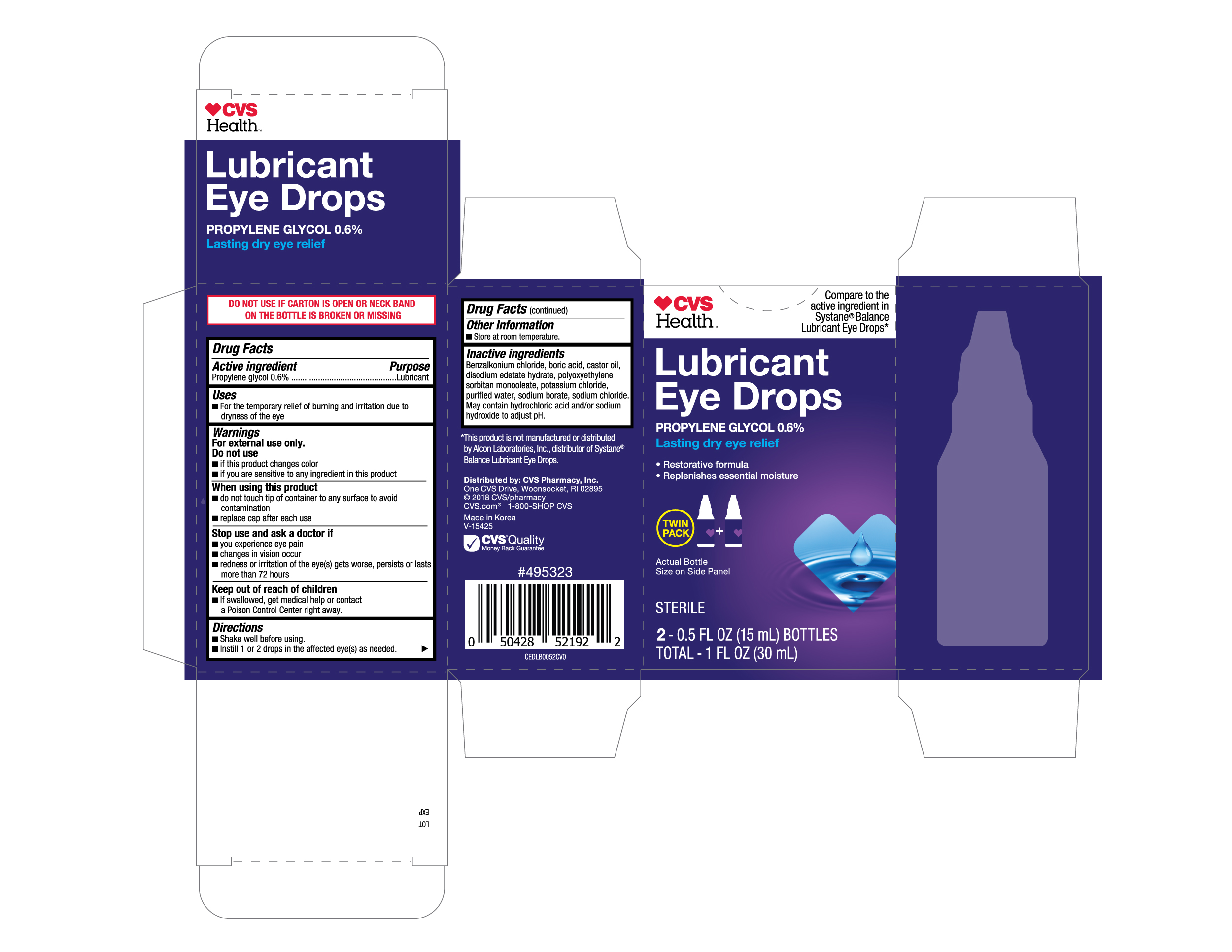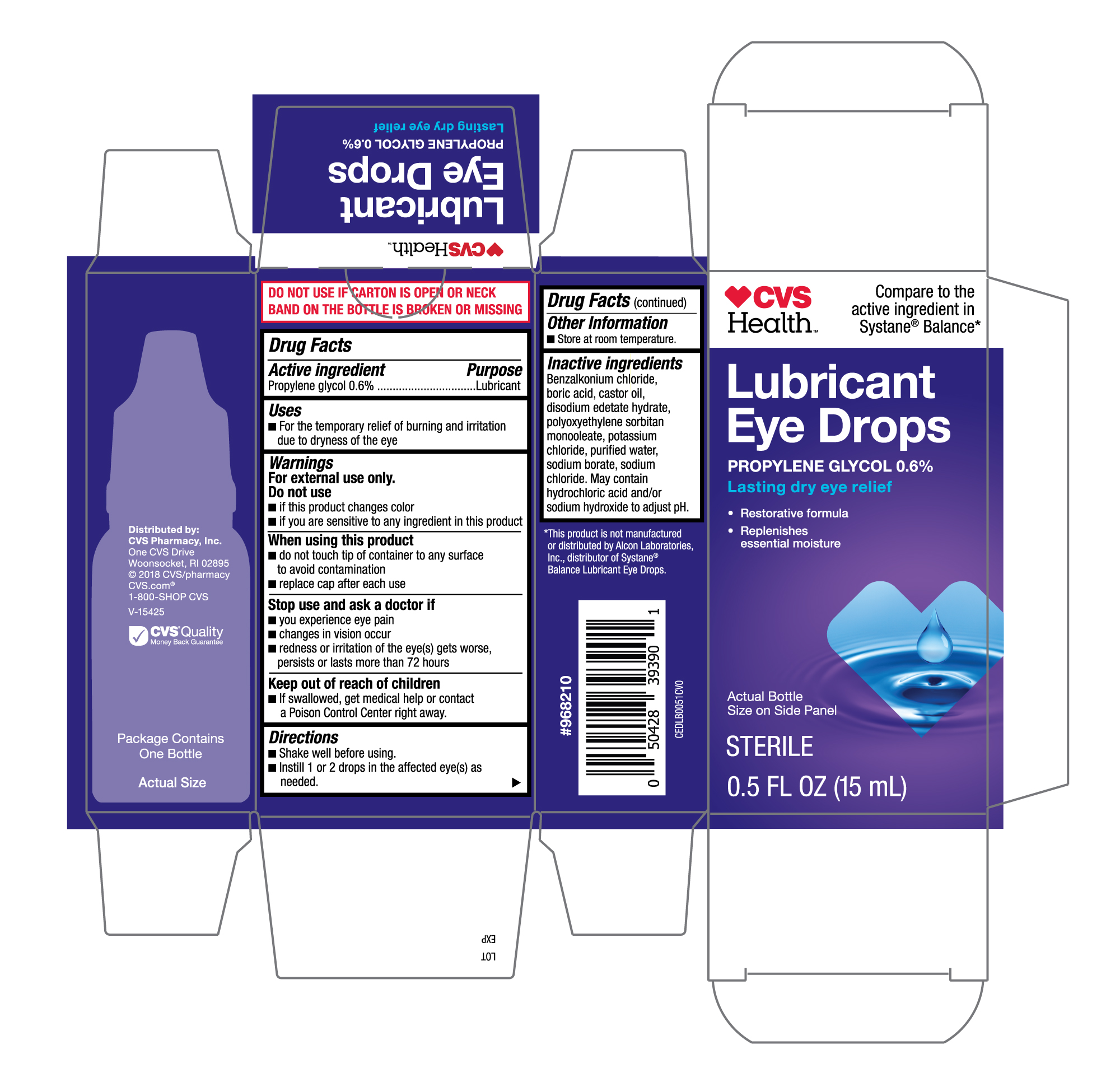 DRUG LABEL: CVS Lubricant Eye Drops 15mL
NDC: 69842-446 | Form: SOLUTION/ DROPS
Manufacturer: CVS Pharmacy, Inc.
Category: otc | Type: HUMAN OTC DRUG LABEL
Date: 20251230

ACTIVE INGREDIENTS: PROPYLENE GLYCOL 0.6 g/100 mL
INACTIVE INGREDIENTS: EDETATE DISODIUM; POTASSIUM CHLORIDE; SODIUM CHLORIDE; HYDROCHLORIC ACID; PEG-6 SORBITAN OLEATE; WATER; CASTOR OIL; SODIUM BORATE; SODIUM HYDROXIDE; BENZALKONIUM CHLORIDE; BORIC ACID

CVS Lubricant Eye Drops 15mL (PLD)

Active ingredient

Propylene glycol 0.6%

Purpose

Lubricant

Uses

- For the temporary relief of burning and irritaion due to dryness of the eye

Warnings

For external use only.

Do not use

- if this product changes color
- if you are sensative to any ingredient in this product

When using this product

- do not touch tip of container to any surface to avoid contamination
- replace cap after each use

Stop use and ask a doctor if

- you experience eye pain
- changes in vision occur
- redness or irritation of the eye(s) gets worse, persists or lasts more than 72 hours

Keep out of reach of children.

- If swallowed, get medical help or contact a Poison Control Center right away.

Directions

- shake well befor using.
- instill 1 or 2 drops in the affected eye(s) as needed.

Other information

- Store at room temperature.

Inactive ingredients

Benzalkonium chloride, boric acid, castor oil, disodium edetate hydrate, polyoxyethylene sorbitan monooleate, potassium chloride, purified water, sodium borate, sodium chloride. May contain hydrochloric acid and/or sodium hydroxide to adjust pH.